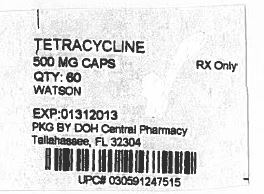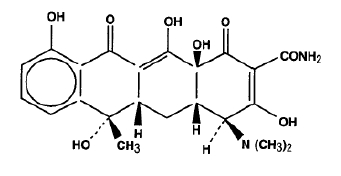 DRUG LABEL: Tetracycline Hydrochloride
NDC: 53808-0877 | Form: CAPSULE
Manufacturer: State of Florida DOH Central Pharmacy
Category: prescription | Type: HUMAN PRESCRIPTION DRUG LABEL
Date: 20130930

ACTIVE INGREDIENTS: TETRACYCLINE HYDROCHLORIDE 500 mg/1 1
INACTIVE INGREDIENTS: LACTOSE; MAGNESIUM STEARATE; SODIUM LAURYL SULFATE; D&C YELLOW NO. 10; FD&C BLUE NO. 1; FD&C RED NO. 40; GELATIN; TITANIUM DIOXIDE; BENZYL ALCOHOL; BUTYLPARABEN; EDETATE CALCIUM DISODIUM; FD&C YELLOW NO. 6; METHYLPARABEN; PROPYLPARABEN; COLLOIDAL SILICON DIOXIDE; SODIUM PROPIONATE; DIMETHICONE; WATER; ALCOHOL; ETHYLENE GLYCOL MONOETHYL ETHER; SHELLAC; LECITHIN, SOYBEAN

TETRACYCLINE
HYDROCHLORIDE
CAPSULES, USP

Description:

Tetracycline is a yellow, odorless, crystalline powder. Tetracycline is stable in air but exposure to strong sunlight causes it to darken. Its potency is affected in solutions of pH below 2 and is rapidly destroyed by alkali hydroxide solutions.

Tetracycline is very slightly soluble in water, freely soluble in dilute acid and in alkali hydroxide solutions, sparingly soluble in alcohol, and practically insoluble in chloroform and in ether.

Each capsule, for oral administration, contains tetracycline hydrochloride 250 mg or 500 mg.

Inactive Ingredients: Lactose, magnesium stearate, and sodium lauryl sulfate.

The 250 mg capsule shell contains D&C Yellow No. 10, FD&C Yellow No. 6, gelatin, sodium lauryl sulfate, and titanium dioxide. It may also contain benzyl alcohol, butylparaben, D&C Red No. 22, edentate calcium disodium, methylparaben, propylparaben, silicon dioxide, and sodium propionate.

The imprinting ink for the 250 mg capsule contains pharmaceutical glaze, and synthetic black iron oxide. It may also contain D&C Yellow No. 10 (aluminum lake), dimethylpolysiloxane, distilled water, ethylene glycol monoethyl ether, FD&C Blue No. 1 (aluminum lake), FD&C Blue No. 2 (aluminum lake), FD&C Red No. 40 (aluminum lake), lecithin, n-butyl alcohol, propylene alcohol, and SDA-3A alcohol.

The 500 mg capsule shell contains D&C Yellow No. 10, FD&C Blue No.1, FD&C Red No. 40, gelatin, sodium lauryl sulfate, and titanium dioxide. It may also contain benzyl alcohol, butylparaben, edetate calcium disodium, FD&C yellow no. 6, methylparaben, propylparaben, silicon dioxide, and sodium propionate.

The imprinting ink for the 500 mg capsule contains titanium dioxide. It may also contain dimethyl polysiloxane, distilled water, ethyl alcohol, ethylene glycol monoethyl ether, pharmaceutical glaze, pharmaceutical shellac, and soya lecithin.

The structural formula is represented below:

C22H24N2O8 Molecular Weight: 444.44

The chemical name for tetracycline hydrochloride is 4-(Dimethylamino)- 1,4,4a,5,5a,6,11,12a-octahydro-3,6,10,12,12a-pentahydroxy-6-methyl 1,11-dioxo-2-naphthacenecarboxamide monohydrochloride.

Clinical Pharmacology:

Tetracyclines are readily absorbed and are bound to plasma protein in varying degrees. They are concentrated by the liver in the bile and excreted in the urine and feces at high concentrations in a biologically active form.

Microbiology:

Tetracyclines are primarily bacteriostatic and exert their antimicrobial effect by the inhibition of protein synthesis. Tetracycline is active against a wide range of gram-negative and gram-positive organisms. The drugs in the tetracycline class have closely similar antimicrobial spectra, and cross-resistance among them is common.

While invitro studies have demonstrated the susceptibility of most strains of the following microorganisms, clinical efficacy for infections other than those included in the INDICATIONS AND USAGE section has not been documented.

Gram-Negative Bacteria:

Neisseria gonorrhea

Haemophilus ducreyi

Haemophilus influenzae

Yersinia pestis (formerly Pasteurellapestis)

Francisella tularensis (formerly Pasterurella tularensis)

Vibrio cholera (formerly Vibrio comma)

Bartonella bacilliformis

Brucella species

Because many strains of the following groups of gram-negative microorganisms have been shown to be resistant to tetracyclines, culture and susceptibility testing are recommended:

Escherichia coli

Klebsiella species

Enterobacter aerogenes

Shigella species

Acinetobacter species (formerly Mima species and Herellea species)

Bacteroides species

Gram-Positive Bacteria:

Because many strains of the following groups of gram-positive microorganisms have been shown to be resistant to tetracycline, culture and susceptibility testing are recommended. Up to 44 percent of strains of Streptococcus pyogenes and 74 percent of Streptococcus faecalis have been found to be resistant to tetracycline drugs. Therefore, tetracyclines should not be used for streptococcal disease unless the organisms have been demonstrated to be susceptible.

Streptococcus pyogenes

Streptococcus pneumoniae

Enterococcus group (Streptococcusfaecalis and Streptococcusfaecium)

Alpha-hemolytic Streptococci (viridans group)

Other Microorganisms:

Chlamydia psittaci

Chlamydia trachomatis

Ureaplasma urealyticum

Borrelia recurrentis

Treponema pallidum

Treponema pertenue

Clostridia species

Fusobacterium fusiforme

Actinomyces species

Bacillus anthraxis

Propionibacterium acnes

Entamoeba species

Balantidium coli

Susceptibility Testing:

A tetracycline disk may be used to determine microbial susceptibility to drugs in the tetracycline class. If the Kirby-Bauer method of disk susceptibility testing is used, a 30 mcg tetracycline disk should give a zone of at least 19 mm when tested against a tetracycline susceptible bacterial strain. Microorganisms may be considered susceptible if the MIC (minimum inhibitory concentration) is not more than 4.0 mcg/mL and intermediate if the MIC is 4.0 to 12.5 mcg/mL.

Indications and Usage:

Tetracycline is indicated in the treatment of infections caused by susceptible strains of the designated organisms in the conditions listed below:

- Upper respiratory tract infections caused by Streptococcuspyogenes, Streptococcuspneumoniae and Hemophilusinfluenzae.
  Note: Tetracycline should not be used for streptococcal disease unless the organism has been demonstrated to be susceptible.
- Lower respiratory tract infections caused by Streptococcuspyogenes, Streptococcuspneumoniae, Mycoplasmapneumoniae (Eaton agent, and Klebsiellasp.)
- Skin and soft tissue infections caused by Streptococcuspyogenes, Staphylococcusaureaus.
  (Tetracyclines are not the drugs of choice in the treatment of any type of staphylococcal infections.)
- Infections caused by rickettsia including Rocky Mountain spotted fever, typhus group infections, Q fever, rickettsialpox.
- Psittacosis of ornithosis caused by Chlamydiapsittaci.
- Infections caused by Chlamydiatrachomatis such as uncomplicated urethral, endocervical, or rectal infections, inclusion conjunctivitis, trachoma and lymphogranuloma venereum.
- Granuloma inquinale caused by Calymmatobacteriumgranulomatis.
- Relapsing fever caused by Borrelia sp.
- Bartonellosis caused by Bartonellabacilli-formis.
- Chancroid caused by Hemophilus ducreyi.
- Tularemia caused by Francisella tularensis.
- Plaque caused by Yersiniapestis.
- Cholera caused by Vibriocholerae.
- Brucellosis caused by Brucella species (tetracycline may be used in conjunction with an aminoglycoside).
- Infections due to Campylobacterfetus.
- As adjunctive therapy in intestinal amebiasis caused by Entamoebahistolytica.
- Urinary tract infections caused by susceptible strains of Escherichia coli, Klebsiella, etc.
- Other infections caused by susceptible gram-negative organisms such as E. coli, Enterobacteraerogenes, Shigella sp., Acinetobacter sp., Klebsiella sp., and Bacteroides sp.
- In severe acne, adjunctive therapy with tetracycline may be useful.

When penicillin is contraindicated, tetracyclines are alternative drugs in the treatment of the following infections:

- syphilis and yaws caused by Treponema pallidumand pertenue, respectively,
- Vincent’s infection caused by Fusobacterium fusiforme,
- infections caused by Neisseria gonorrhoeae,
- anthrax caused by Bacillus anthracis,
- infections due to Listeria monocytogenes,
- actinomycosis caused by Actinomyces species,
- infections due to Clostridium species.

Contraindications:

This drug is contraindicated in persons who have shown hypersensitivity to any of the tetracyclines.

Warnings:

THE USE OF DRUGS OF THE TETRACYCLINE CLASS DURING TOOTH DEVELOPMENT (LAST HALF OF PREGNANCY, INFANCY AND CHILDHOOD TO THE AGE OF 8 YEARS) MAY CAUSE PERMANENT DISCOLORATION OF THE TEETH (YELLOW-GRAY-BROWN). This adverse reaction is more common during long-term use of the drugs but has been observed following repeated short-term courses. Enamel hypoplasia has also been reported. TETRACYCLINE DRUGS, THEREFORE, SHOULD NOT BE USED IN THIS AGE GROUP UNLESS OTHER DRUGS ARE NOT LIKELY TO BE EFFECTIVE OR ARE CONTRAINDICATED.

All tetracyclines form a stable calcium complex in any bone forming tissue. A decrease in fibula growth rate has been observed in premature infants given oral tetracycline in doses of 25 mg/kg every six hours. This reaction was shown to be reversible when the drug was discontinued.

Results of animal studies indicate that tetracyclines cross the placenta, are found in fetal tissues and can have toxic effects on the developing fetus (often related to retardation of skeletal development). Evidence of embryotoxicity has also been noted in animals treated early in pregnancy. If this drug is used during pregnancy or if the patient becomes pregnant while taking this drug, the patient should be apprised of the potential hazard to the fetus. Tetracycline drugs should not be used during pregnancy unless absolutely necessary.

If renal impairment exists, even usual oral or parenteral doses may lead to excessive systemic accumulation of the drug and possible liver toxicity. Under such conditions, lower than usual total doses are indicated, and, if therapy is prolonged, serum level determinations of the drug may be advisable.

Photosensitivity manifested by an exaggerated sunburn reaction has been observed in some individuals taking tetracyclines. Patients apt to be exposed to direct sunlight or ultraviolet lights should be advised that this reaction can occur with tetracycline drugs. Treatment should be discontinued at the first evidence of skin erythema.

The antianabolic action of the tetracyclines may cause an increase in BUN. While this is not a problem in those with normal renal function, in patients with significantly impaired renal function, higher serum levels of tetracycline may lead to azotemia, hyperphosphatemia and acidosis.

Precautions:

General:

As with other antibiotics, use of this drug may result in overgrowth of nonsusceptible organisms, including fungi. If superinfection occurs, the antibiotic should be discontinued and appropriate therapy should be instituted.

All infections due to Group A betahemolytic streptococci should be treated for at least ten days.

Bulging fontanels in infants and benign intracranial hypertension in adults have been reported in individuals receiving tetracyclines. These conditions disappeared when the drug was discontinued.

Incision and drainage or other surgical procedures should be performed in conjunction with antibiotic therapy, when indicated.

Laboratory Tests:

In venereal diseases, when coexistent syphilis is suspected, dark field examinations should be done before treatment is started and the blood serology repeated monthly for at least four months.

In long-term therapy, periodic laboratory evaluation of organ systems, including hematopoietic, renal and hepatic studies, should be performed.

Drug Interactions:

Since bacteriostatic drug may interfere with the bactericidal action of penicillin, it is advisable to avoid giving tetracycline in conjunction with penicillin or other bactericidal antibiotics.

Because the tetracyclines have been shown to depress plasma prothrombin activity, patients who are on anticoagulant therapy may require downward adjustment of their anticoagulant dosage.

The concurrent use of tetracycline and methoxyflurane has been reported to result in fatal renal toxicity.

Absorption of tetracyclines is impaired by antacids containing aluminum, calcium or magnesium and preparations containing iron, zinc, or sodium bicarbonate.

Concurrent use of tetracycline may render oral contraceptives less effective.

Carcinogenesis, Mutagenesis, Impairment of Fertility:

Long-term animal studies are currently being conducted to determine whether tetracycline hydrochloride has carcinogenic potential. Some related antibiotics (oxytetracycline, minocycline) have shown evidence of oncogenic activity in rats.

In two in vitro mammalian cell assay systems (L 51784y mouse lymphoma and Chinese hamster lung cells), there was evidence of mutagenicity at tetracycline hydrochloride concentrations of 60 and 10 µg/mL, respectively.

Tetracycline hydrochloride had no effect on fertility when administered in the diet to male and female rats at a daily intake of 25 times the human dose.

Teratogenic Effects:

Category D: (See WARNINGS.)

Nonteratogenic Effects:

(See WARNINGS.) Pregnant women with renal disease may be more prone to develop tetracycline-associated liver failure.

Labor and Delivery:

The effect of tetracyclines on labor and delivery is unknown.

Nursing Mothers:

Because of potential for serious adverse reaction in nursing infants from tetracyclines, a decision should be made whether to discontinue the drug, taking into account the importance of the drug to the mother (see WARNINGS).

Pediatric Use:

See WARNINGS and DOSAGE AND ADMINISTRATION.

Adverse Reactions:

Gastrointestinal:

Anorexia, nausea, epigastric distress, vomiting, diarrhea, glossitis, black hairy tongue, dysphagia, enterocolitis, and inflammatory lesions (with monilial overgrowth) in the anogenital region.

Rare instances of esophagitis and esophageal ulceration have been reported in patients receiving particularly the capsule and also the tablet forms of tetracyclines. Most of the patients were reported to have taken medication immediately before going to bed (see DOSAGE AND ADMINISTRATION section).

Teeth:

Permanent discoloration of teeth may be caused during tooth development. Enamel hypoplasia has also been reported (see WARNINGS).

Skin:

Maculopapular and erythrematous rashes. Exfoliative dermatitis has been reported but is uncommon. Onycholysis and discoloration of the nails have been reported rarely. Photosensitivity is discussed in WARNINGS .

Renal Toxicity:

Rise in BUN has been reported and is apparently dose related.

Liver:

Hepatotoxicity and liver failure have been observed in patients receiving large doses of tetracycline and tetracyclinetreated patients with renal impairment.

Hypersensitivity Reactions:

Urticaria, angioneurotic edema, anaphylaxis, anaphylactoid purpura, pericarditis, exacerbation of systemic lupus erythematosus, and serum sickness-like reactions, as fever, rash, and arthralgia.

Blood:

Hemolytic anemia, thrombocytopenia, thrombocytopenic purpura, neutropenia and eosinophilia have been reported.

Other:

Bulging fontanels in infants and intracranial pressure in adults (see PRECAUTIONS— General).

When given over prolonged periods, tetracyclines have been reported to produce brown-black microscopic discoloration of thyroid glands. No abnormalities of thyroid function studies are known to occur.

OVERDOSAGE:

In case of overdosage, discontinue medication, treat symptomatically and institute supportive measures. Tetracycline is not dialyzable.

Dosage and Administration:

Adults:

Usual daily dose, 1 gram as 500 mg b.i.d. or 250 mg q.i.d. Higher doses such as 500 mg q.i.d. may be required for severe infections or for those infections which do not respond to the smaller doses.

Children above eight years of age:

Usual daily dose, 10 to 20 mg/lb (25 to 50 mg/kg) body weight divided in four equal doses.

Therapy should be continued for at least 24 to 48 hours after symptoms and fever have subsided.

For the treatment of brucellosis, 500 mg tetracycline q.i.d. for three weeks should be accompanied by streptomycin, 1 gram intramuscularly twice daily the first week and once daily the second week.

For the treatment of syphilis in patients allergic to penicillin, the following dosage of tetracycline is recommended: early syphilis (less than one year’s duration) —500 mg q.i.d. for 15 days. Syphilis of more than one year’s duration (except neurosyphilis)—500 q.i.d. for 30 days.

For treatment of gonorrhea, the recommended dose is 500 mg by mouth four times a day for seven days.

In cases of moderate to severe acne which, in the judgement of the clinician, require long-term treatment, the recommended initial dosage is 1 gram daily in divided doses. When improvement is noted, dosage should be gradually reduced to maintenance levels ranging from 125 mg to 500 mg daily. In some patients it may be possible to maintain adequate remission of lesions with alternate day or intermittent therapy. Tetracycline therapy of acne should augment the other standard measures known to be of value. Duration of long-term treatment which can safely be recommended has not been established (see WARNINGS and Carcinogenesis, Mutagenesis, Impairment of Fertility).

Concomitant Therapy:

Absorption of tetracyclines is impaired by antacids containing aluminum, calcium or magnesium and preparations containing iron, zinc or sodium bicarbonate.

Food and some dairy products also interfere with absorption.

In the treatment of streptococcal infections, a therapeutic dose of tetracycline should be administered for at least ten days.

In patients with renal impairment (see WARNINGS) total dosage should be decreased by reduction of recommended individual doses and/or by extending time intervals between doses.

Uncomplicated urethral, endocervical or rectal infections in adults caused by Chlamydiatrachomatis: 500 mg, by mouth, four times a day for at least seven days.

Administration of adequate amounts of fluid with the capsule formulation of tetracycline is recommended to wash down the drug and reduce the risk of esophageal irritation and ulceration (see ADVERSE REACTIONS).

How Supplied:

Tetracycline Hydrochloride Capsules, USP are supplied by State of Florida DOH Central Pharmacy as follows:

NDC | Strength | Quantity/Form | Color | Source Prod. Code
53808-0877-2 | 500 mg | 60 Capsules in a Blister Pack | Yellow Opaque Body | 0591-2475

Store at 20°-25°C (68°-77°F). [See USP Controlled Room Temperature].

ANIMAL PHARMACOLOGY AND ANIMAL TOXICOLOGY:

Hyperpigmentation of the thyroid has been produced by members of the tetracycline class in the following species: in rats by oxytetracycline, doxycycline, tetracycline PO4 and methacycline; in minipigs by doxycycline, minocycline, tetracycline PO4 and methacycline; in dogs by doxycycline and minocycline; in monkeys by minocycline.

Minocycline, tetracycline PO4, methacycline, doxycycline, tetracycline base, oxytetracycline HCl and tetracycline HCl were goitrogenic in rats fed a low iodine diet. This goitrogenic effect was accomplished by high radioactive iodine uptake.

Administration of minocycline also produced a large goiter with high radioiodine uptake in rats fed a relatively high iodine diet.

Treatment of various animal species with this class of drugs has also resulted in the induction of thyroid hyperplasia in the following: in rats and dogs (minocycline), in chickens chlortetracycline) and in rats and mice (oxytetracycline). Adrenal gland hyperplasia has been observed in goats and rats treated with oxytetracycline.

Manufactured By:
Watson Pharma Private Limited
Verna, Salcette Goa 403 722 INDIA
Distributed By:
Watson Pharma, Inc.
Corona, CA 92880 USA

This Product was Repackaged By:

State of Florida DOH Central Pharmacy
104-2 Hamilton Park Drive
Tallahassee, FL 32304
United States

PACKAGE LABEL

Label Image for 53808-0877
500mg